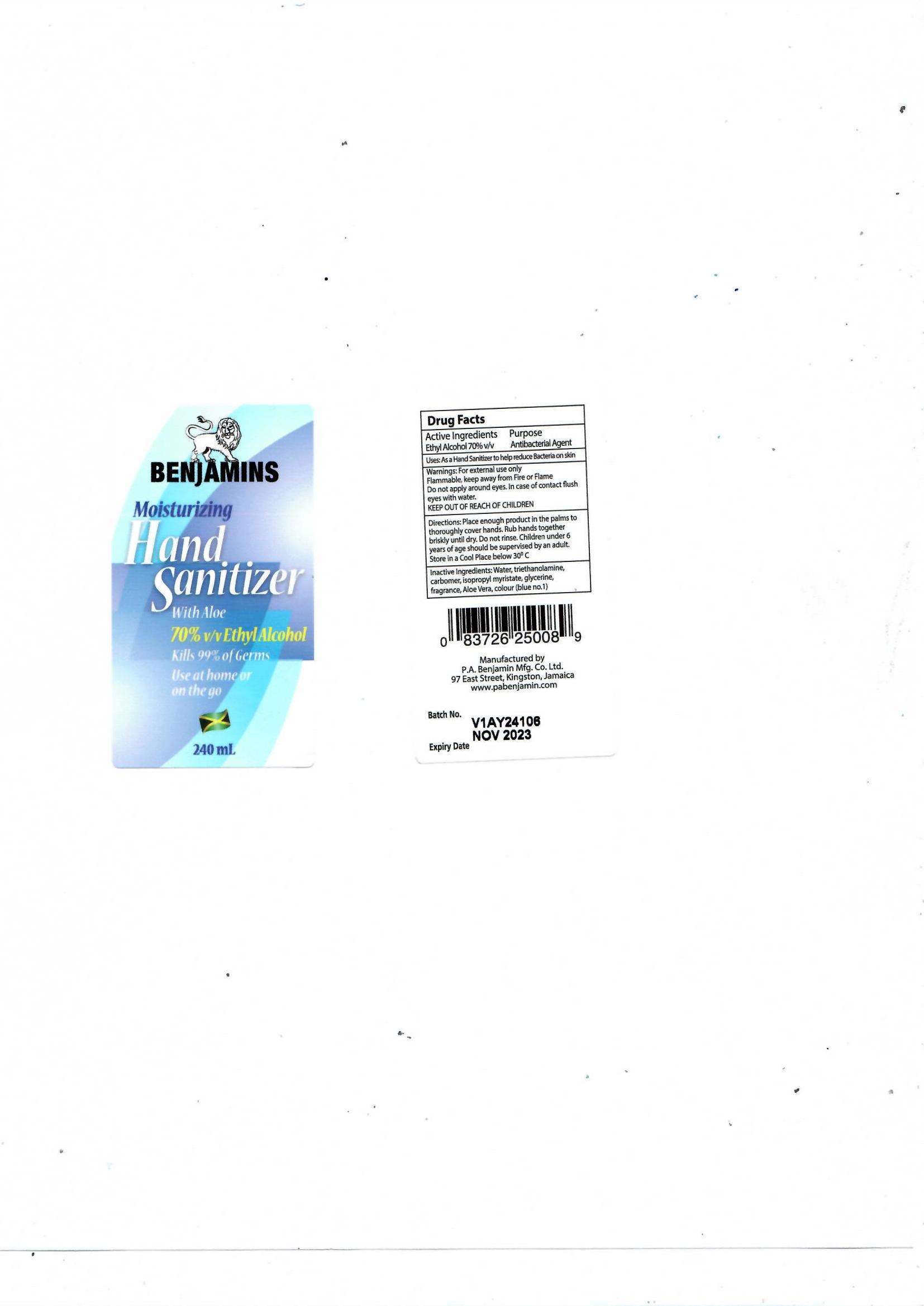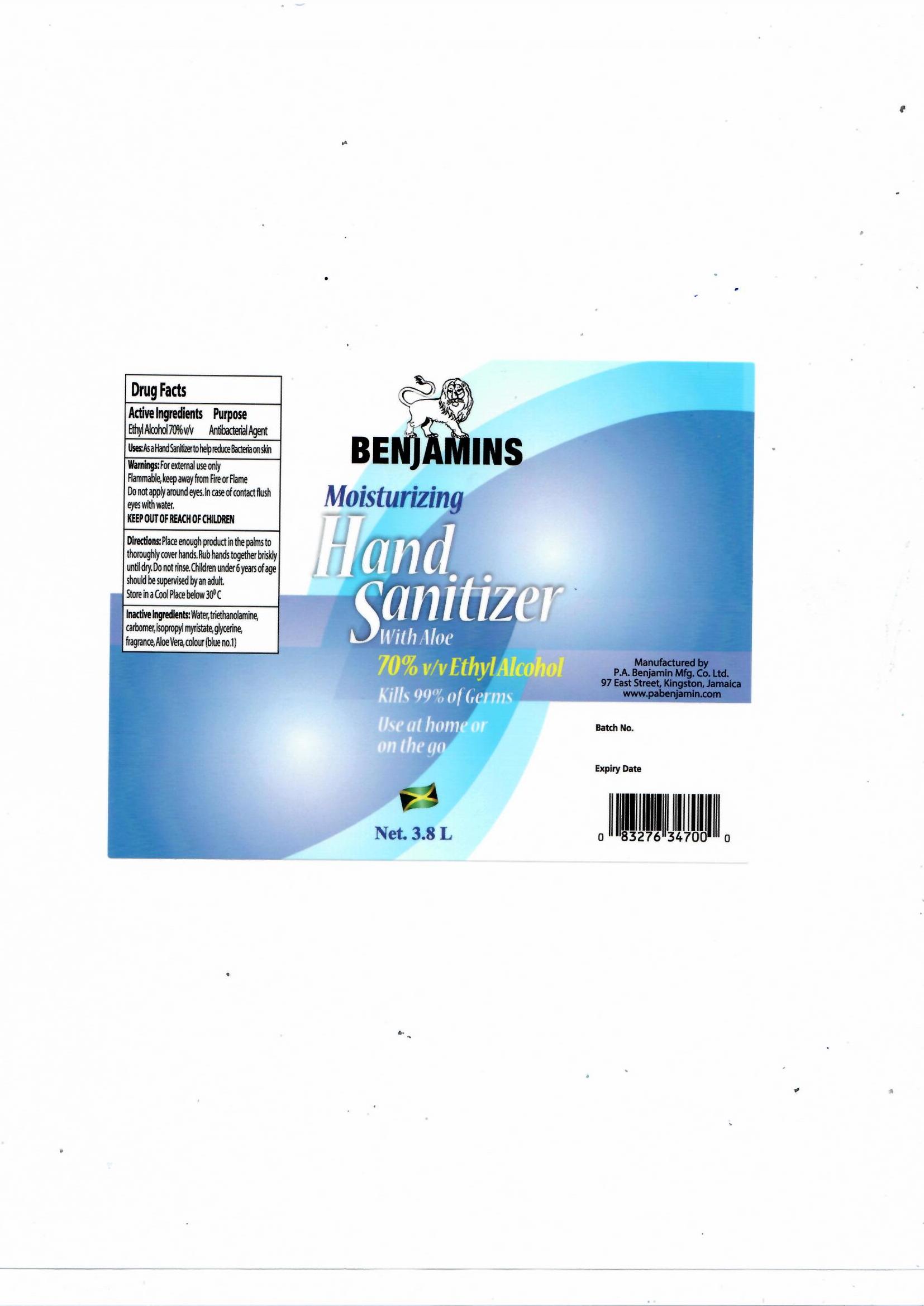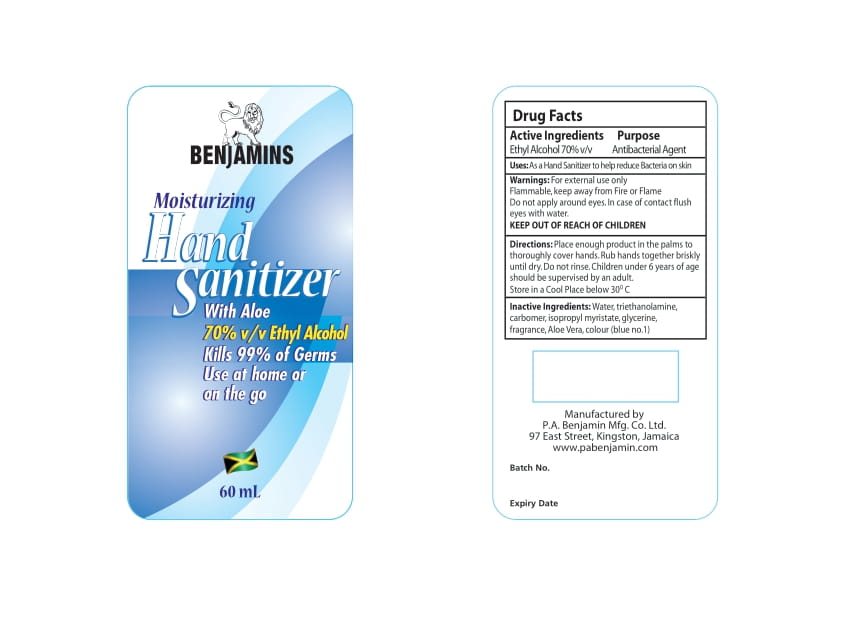 DRUG LABEL: Benjamins Hand Sanitizer
NDC: 82338-438 | Form: GEL
Manufacturer: P. A BENJAMIN MANUFACTURING CO LTD
Category: otc | Type: HUMAN OTC DRUG LABEL
Date: 20211231

ACTIVE INGREDIENTS: ALCOHOL 459.96 mL/1000 mL
INACTIVE INGREDIENTS: POGOSTEMON CABLIN LEAF OIL; HYDROXYISOHEXYL 3-CYCLOHEXENE CARBOXALDEHYDE; DIHYDROMYRCENOL; GRAPEFRUIT OIL; 2-ISOBUTYL-4-METHYLTETRAHYDROPYRAN-4-OL; ETHYL LINALOOL; 3-(3,4-METHYLENEDIOXYPHENYL)-2-METHYLPROPANAL; BENZYL SALICYLATE; 3-HEXENYL SALICYLATE, CIS-; GLYCERIN 1.98 mL/1000 mL; ISOPROPYL MYRISTATE 3.05 mL/1000 mL; WATER; CARBOMER 940 3.6 g/1000 mL; FD&C BLUE NO. 1 0.0002 g/1000 mL; TROLAMINE 4.82 mL/1000 mL; ALOE VERA LEAF 0.116 g/1000 mL; ETHYLENE BRASSYLATE; ISOCYCLEMONE E; LINALOOL, (+/-)-; LINALYL ACETATE; BUTYLPHENYL METHYLPROPIONAL; .ALPHA.-HEXYLCINNAMALDEHYDE; METHYL DIHYDROJASMONATE (SYNTHETIC)

Benjamins Hand Sanitizer

Active Ingredient(s)

Ethyl Alcohol 70% v/v.

Purpose

Purpose: Antiseptic/ Antibacterial Agent

Use

As a Hand Sanitizer to help reduce bacteria on skin.

Warnings

For external use only. Flammable.

Keep away from heat or flame.

Do not apply around eyes. In case of contact flush eyes with water.

KEEP OUT OF REACH OF CHILDREN.

Do not use

- Do not apply around eyes. In case of contact flush eyes with water.

WHEN USING

Do not apply around eyes. In case of contact flush eyes with water.

KEEP OUT OF THE REACH OF CHILDREN.

Children under 6 years of age should be supervised by an adult.

Directions

Place enough product in the palms to thoroughly cover hands. Rub hands together briskly until dry. Do not rinse. Children under 6 years of age should be supervised by an adult.

Other information

- Store in a Cool Place below 30OC.

Inactive ingredients

Water, triethanolamine, carbomer, isopropyl myristate, glycerine, fragrance, Aloe Vera, Colour (Blue no.1)

Package Label - Principal Display Panel for Benjamins Hand Sanitizer 60 mL

Benjamins Hand Sanitizer 60 mL NDC: 82338-438-60

Package Label - Principal Display Panel for Benjamins Hand Sanitizer 240 mL

Benjamins 240 mL Hand Sanitizer. NDC : 82338-438-24

Package Label - Principal Display Panel for Benjamins Hand Sanitizer 3.8 Lt

Benjamins Hand Sanitizer 3.8 Lt. NDC: 82338-438-3.8